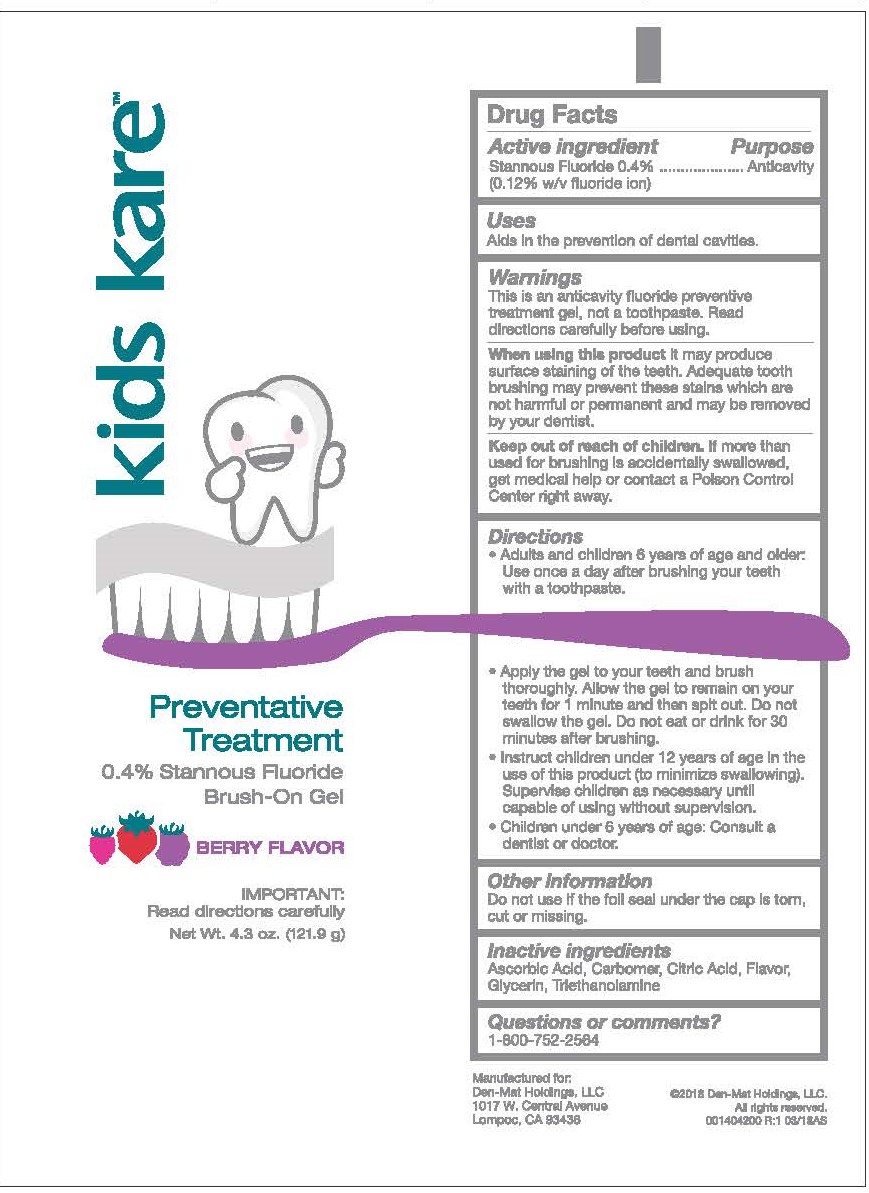 DRUG LABEL: kids kare
NDC: 59883-404 | Form: GEL
Manufacturer: DEN-MAT HOLDINGS, LLC.
Category: otc | Type: HUMAN OTC DRUG LABEL
Date: 20241231

ACTIVE INGREDIENTS: STANNOUS FLUORIDE 0.969 mg/1 g
INACTIVE INGREDIENTS: CARBOMER HOMOPOLYMER TYPE B (ALLYL SUCROSE CROSSLINKED); GLYCERIN; TROLAMINE; BERRY; ANHYDROUS CITRIC ACID; ASCORBIC ACID

Kids kare Stannous Fluoride

Active ingredient

Stannous Fluoride 0.4% (0.12% w/v fluoride ion)

Purpose

Anticavity

Uses

Aids in the prevention of dental cavities.

Warnings

This is an anticavity fluoride preventive treatment gel, not a toothpaste. Read directions carefully before using.

WHEN USING

When using this productit may produce surface staining of the teeth, Adequate tooth brushing may prevent these stains which are not harmful or permanent and may be removed by your dentist.

Keep out of reach of children.If more than used for brushing is accidentally swallowed, get medical help or contact a Poison Control Center right away.

Directions

- Adults and children 6 years of age and older: Use once a day after brushing your teeth with a toothpaste.
- Apply the get to your teeth and brush thoroghly. Allow the gel to remain on your teeth for 1 minute and then spit out. Do not swallow the gel. Do not eat or drink for 30 minutes after brushing.
- Instruct children under 12 years of age in the use of this product (to minimize swallowing). Supervise children as necessary until capable of using without supervision.
- Children under 6 years of age: Consult a dentist or doctor.

Other information

Do not use if the foil seal under the cap is torn, cut or missing.

inactive ingredient

Ascorbic Acid, Carbomer, Citric Acid, Flavor, Glycerin, Triethanolamine

Questions or comments?

1-800-752-2564

Principal Display Panel

kids kare™

Preventative Treatment

0.4% Stannous Fluoride

Brush-On Gel

BERRY FLAVOR

IMPORTANT:

Read directions carefully

Net Wt. 4.3 oz. (121.9 g)